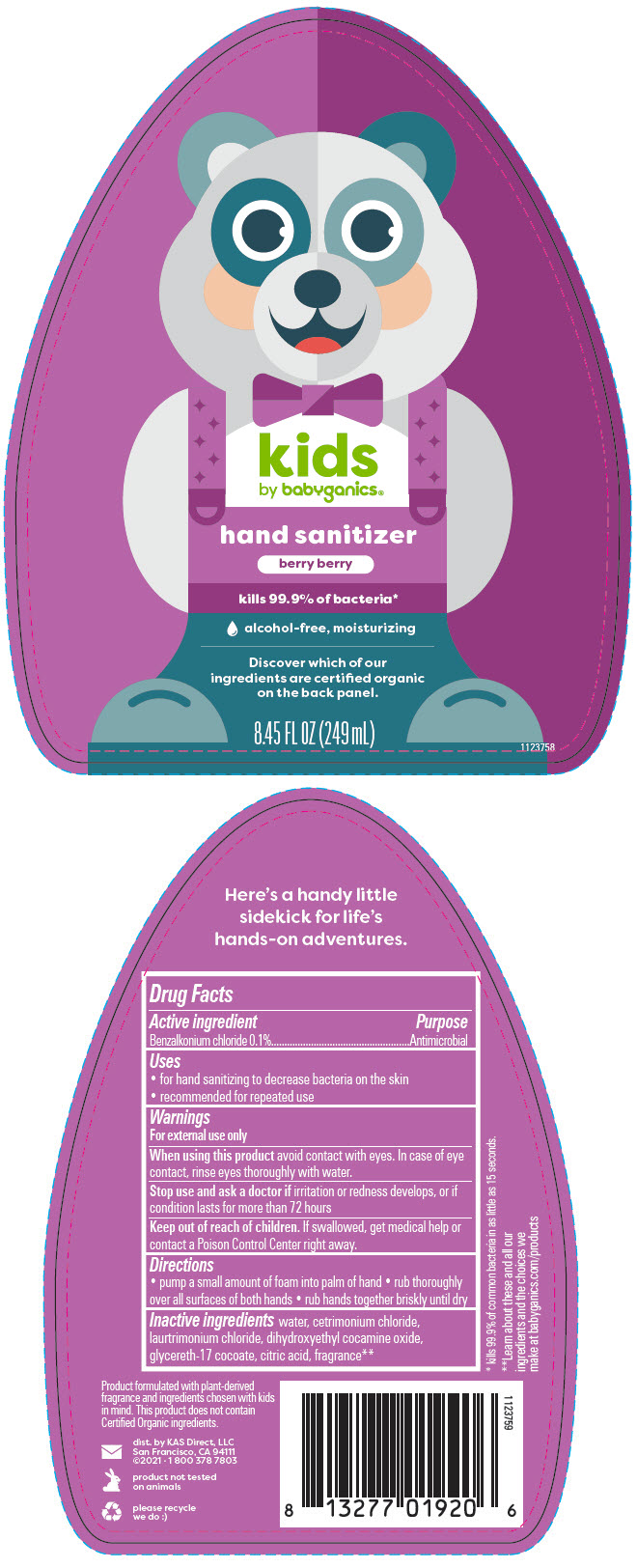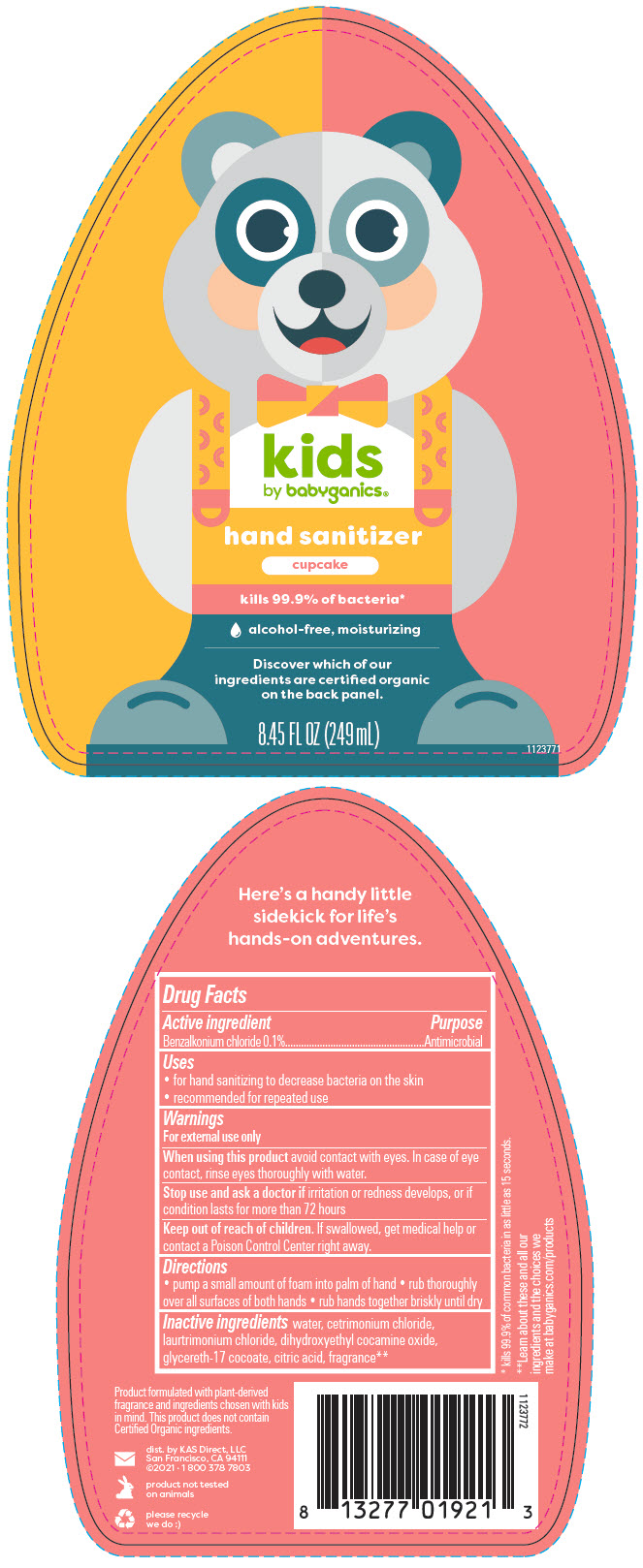 DRUG LABEL: BabyGanics Kids Alcohol Free Foaming Hand Sanitizer Berry Berry
NDC: 59062-4100 | Form: LIQUID
Manufacturer: KAS Direct LLC dba BabyGanics
Category: otc | Type: HUMAN OTC DRUG LABEL
Date: 20251208

ACTIVE INGREDIENTS: BENZALKONIUM CHLORIDE 0.1 mg/1 mL
INACTIVE INGREDIENTS: WATER; CETRIMONIUM CHLORIDE; LAURTRIMONIUM CHLORIDE; DIHYDROXYETHYL COCAMINE OXIDE; GLYCERETH-17 COCOATE; CITRIC ACID MONOHYDRATE

BabyGanics® Kids Alcohol Free Foaming Hand Sanitizer
Liquid

Drug Facts

Active ingredient

Benzalkonium chloride 0.1%

Purpose

Antimicrobial

Uses

- for hand sanitizing to decrease bacteria on the skin
- recommended for repeated use

Warnings

For external use only

When using this product avoid contact with eyes. In case of eye contact, rinse eyes thoroughly with water.

Stop use and ask a doctor if irritation or redness develops, or if condition lasts for more than 72 hours

Keep out of reach of children. If swallowed, get medical help or contact a Poison Control Center right away.

Directions

- pump a small amount of foam into palm of hand
- rub thoroughly over all surfaces of both hands
- rub hands together briskly until dry

Inactive ingredients

water, cetrimonium chloride, laurtrimonium chloride, dihydroxyethyl cocamine oxide, glycereth-17 cocoate, citric acid, fragrance [Learn about these and all our ingredients and the choices we make at babyganics.com/products]

dist. by KAS Direct, LLC
San Francisco, CA 94111

PRINCIPAL DISPLAY PANEL - 249 mL Bottle Label - Berry Berry

kids
by babyganics®

hand sanitizer
berry berry

kills 99.9% of bacteria*

alcohol-free, moisturizing

Discover which of our
ingredients are certified organic
on the back panel.

8.45 FL OZ (249 mL)

1123758

PRINCIPAL DISPLAY PANEL - 249 mL Bottle Label - Cupcake

kids
by babyganics®

hand sanitizer
cupcake

kills 99.9% of bacteria*

alcohol-free, moisturizing

Discover which of our
ingredients are certified organic
on the back panel.

8.45 FL OZ (249 mL)

1123771